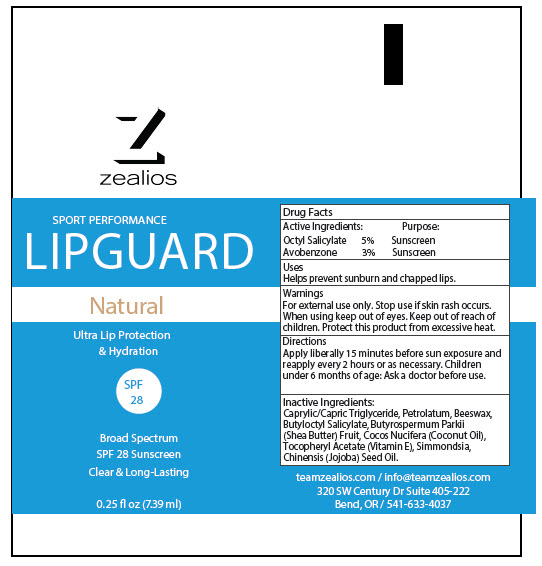 DRUG LABEL: Zealios SPF LipGuard
NDC: 83326-002 | Form: GEL
Manufacturer: Personal Best Products Inc. dba Zealios
Category: otc | Type: HUMAN OTC DRUG LABEL
Date: 20250113

ACTIVE INGREDIENTS: OCTISALATE 50 mg/1 mL; AVOBENZONE 30 mg/1 mL
INACTIVE INGREDIENTS: MEDIUM-CHAIN TRIGLYCERIDES; PETROLATUM; YELLOW WAX; BUTYLOCTYL SALICYLATE; SHEA BUTTER; COCONUT OIL; .ALPHA.-TOCOPHEROL; JOJOBA OIL

Zealios SPF LipGuard

Drug Facts

ACTIVE INGREDIENT

Active Ingredients: | Purpose:
Octyl Salicylate 5% | Sunscreen
Avobenzone 3% | Sunscreen

Uses

Helps prevent sunburn and chapped lips.

Warnings

For external use only. Stop use if skin rash occurs. When using keep out of eyes.

Keep out of reach of children. Protect this product from excessive heat.

Directions

Apply liberally 15 minutes before sun exposure and reapply every 2 hours or as necessary. Children under 6 months of age: Ask a doctor before use.

Inactive Ingredients

Caprylic/Capric Triglyceride, Petrolatum, Beeswax, Butyloctyl Salicylate, Butyrospermum Parkii (Shea Butter) Fruit, Cocos Nucifera (Coconut Oil), Tocopheryl Acetate (Vitamin E), Simmondsia, Chinensis (Jojoba) Seed Oil.

PRINCIPAL DISPLAY PANEL - 7.39 ml Tube Label

zealios

SPORT PERFORMANCE
LIPGUARD

Natural

Ultra Lip Protection
& Hydration

SPF
28

Broad Spectrum
SPF 28 Sunscreen
Clear & Long-Lasting

0.25 fl oz (7.39 ml)